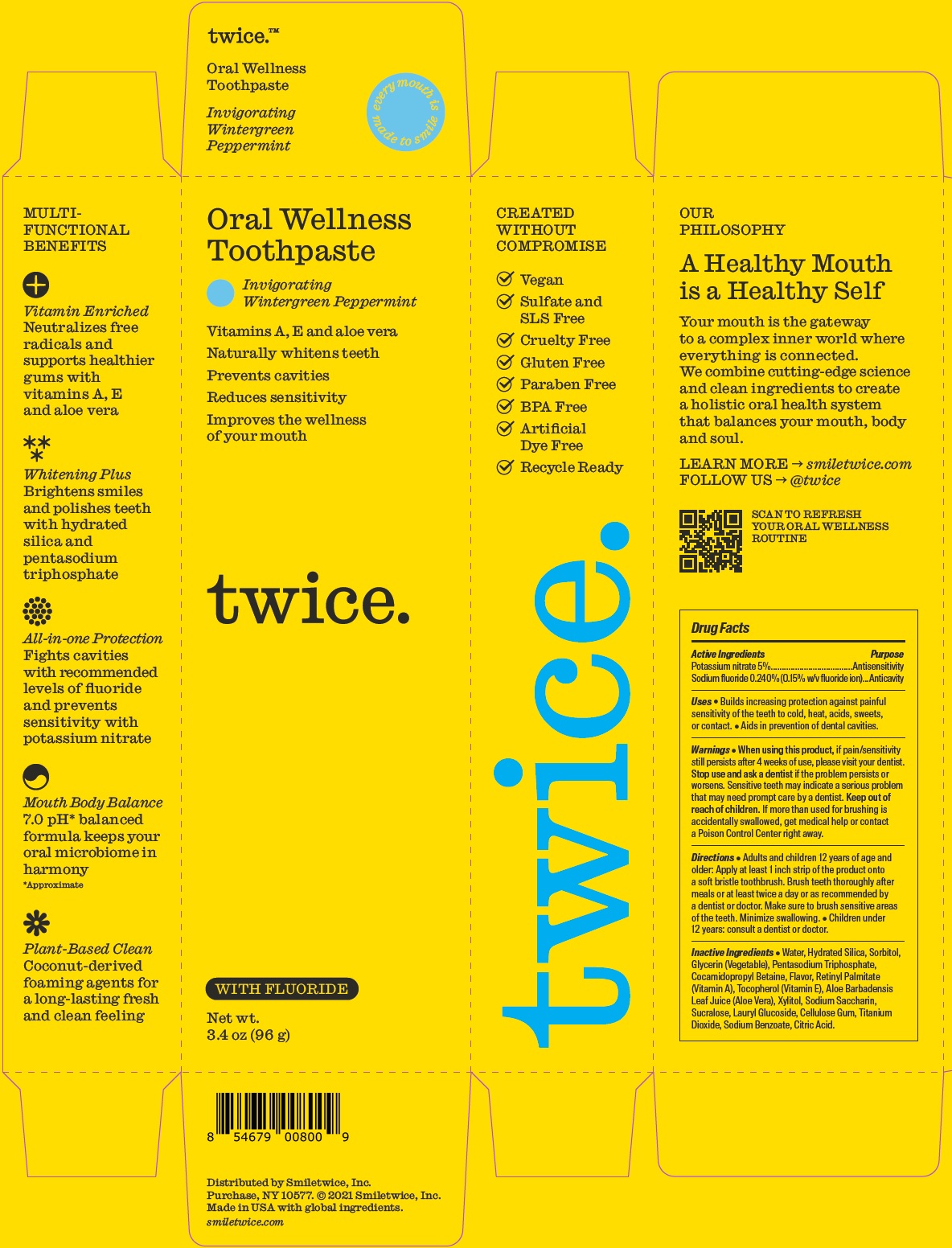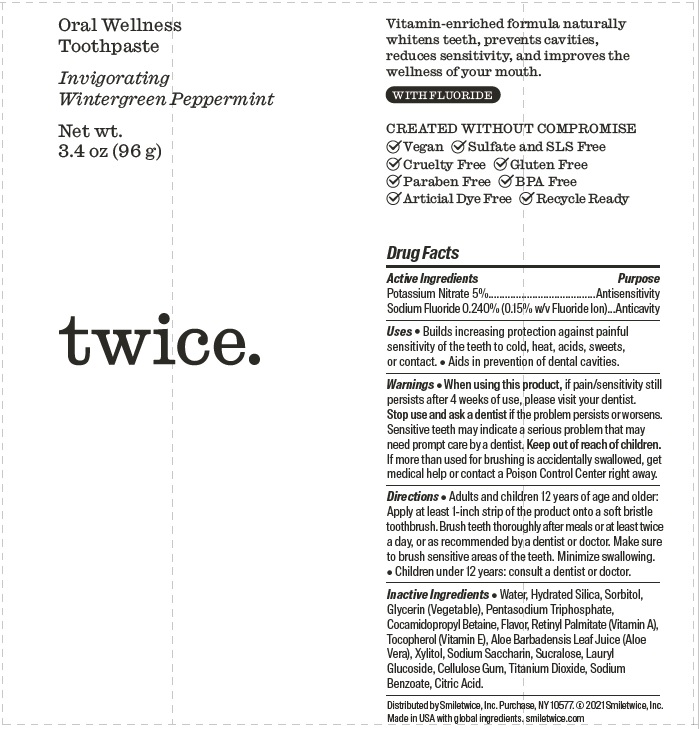 DRUG LABEL: Wintergreen Peppermint
NDC: 72164-005 | Form: PASTE, DENTIFRICE
Manufacturer: Twice Twice LLC
Category: otc | Type: HUMAN OTC DRUG LABEL
Date: 20260119

ACTIVE INGREDIENTS: POTASSIUM NITRATE 50 mg/1 g; SODIUM FLUORIDE 1.5 mg/1 g
INACTIVE INGREDIENTS: WATER; HYDRATED SILICA; SORBITOL; GLYCERIN; SODIUM TRIPOLYPHOSPHATE ANHYDROUS; COCAMIDOPROPYL BETAINE; METHYL SALICYLATE; VITAMIN A PALMITATE; TOCOPHEROL; ALOE VERA LEAF; SACCHARIN SODIUM; SUCRALOSE; LAURYL GLUCOSIDE; CARBOXYMETHYLCELLULOSE SODIUM, UNSPECIFIED; TITANIUM DIOXIDE; SODIUM BENZOATE; CITRIC ACID MONOHYDRATE

Wintergreen Peppermint Toothpaste

Active Ingredients

Potassium nitrate 5%.

Sodium fluoride 0.240% (0.15% w/v fluoride ion).

Purpose

Antisensitivity

Anticavity

Uses

- Builds increasing protection against painful sensitivity of the teeth to cold, heat, acids, sweets, or contact.
- Aids in prevention of dental cavities.

Warnings

When using this product

- if pain/sensitivity still persists after 4 weeks of use, please visit your dentist.

Stop use and ask a dentist

if the problem persists or worsens. Sensitive teeth may indicate a serious problem that may need prompt care by a dentist.

Keep out of reach of children.

If more than used for brushing is accidentally swallowed, get medical help or contact a Poison Control Center right away.

Directions

• Adults and children 12 years of age and older: Apply at least 1 inch strip of the product onto a soft bristle toothbrush. Brush teeth thoroughly after meals or at least twice a day or as recommended by a dentist or doctor. Make sure to brush sensitive areas of the teeth. Minimize swallowing.

• Children under 12 years: consult a dentist or doctor.

Inactive Ingredients

• Water, Hydrated Silica, Sorbitol, Glycerin (Vegetable), Pentasodium Triphosphate, Cocamidopropyl Betaine, Flavor, Retinyl Palmitate (Vitamin A), Tocopherol (Vitamin E), Aloe Barbadensis Leaf Juice (Aloe Vera), Xylitol, Sodium Saccharin, Sucralose, Lauryl Glucoside, Cellulose Gum, Titanium Dioxide, Sodium Benzoate, Citric Acid.